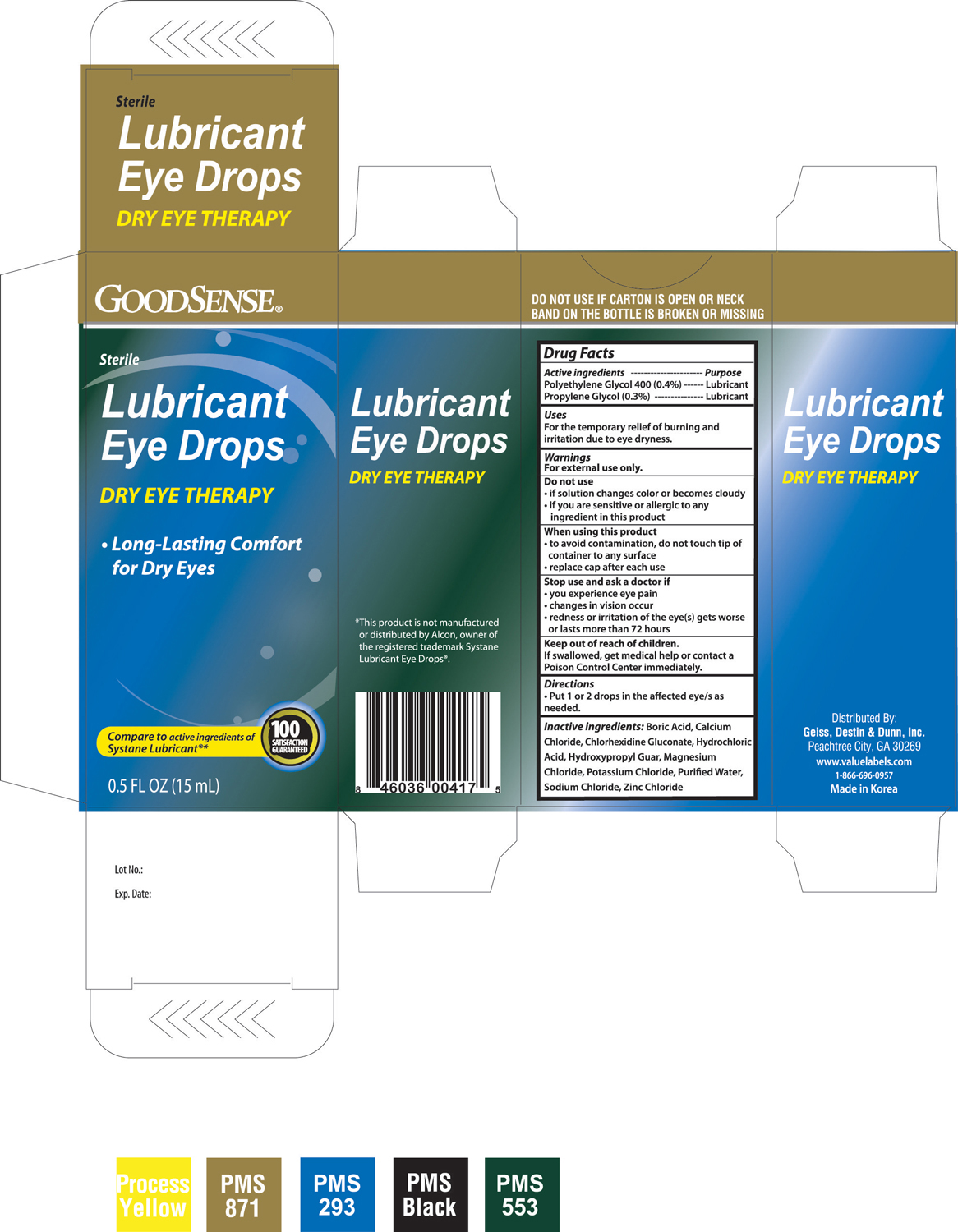 DRUG LABEL: GOODSENSE LUBRICANT EYE DROPS
NDC: 11716-0042 | Form: SOLUTION
Manufacturer: HANLIM PHARM. CO., LTD.
Category: otc | Type: HUMAN OTC DRUG LABEL
Date: 20100804

ACTIVE INGREDIENTS: POLYETHYLENE GLYCOL 400 0.4 mL/1 mL; PROPYLENE GLYCOL 0.3 mL/1 mL
INACTIVE INGREDIENTS: BORIC ACID; CALCIUM CHLORIDE; CHLORHEXIDINE GLUCONATE; HYDROCHLORIC ACID; MAGNESIUM CHLORIDE; POTASSIUM CHLORIDE; WATER; SODIUM CHLORIDE; ZINC CHLORIDE

DRUG FACTS

ACTIVE INGREDIENT

Active ingredients -----------------------------------------------------------------------Purpose

Polyethylene Glycol 400 (0.4%) ---------------------------------------------------Lubricant

Propylene Glycol (0.3%) --------------------------------------------------------------Lubricant

Uses

For the temporary relief of burning and irritation due to eye dryness.

Warnings

For external use only.

Do not use

- if solution changes color or becomes cloudy
- if you are sensitive or allergic to any ingredient in this product

When using this product

- to avoid contamination, do not touch tip of container to any surface
- replace cap after each use

Stop use and ask a doctor if

- you experience eye pain
- changes in vision occur
- redness or irritation of the eye(s) gets worse or lasts more than 72 hours

Keep out of reach of children.

If swallowed, get medical help or contact a Poison Control Center immediately.

Directions

- Put 1 or 2 drops in the affected eye/s as needed.

INACTIVE INGREDIENT

Inactive ingredients: Boric Acid, Calcium Chloride, Chlorhexidine Gluconate, Hydrochloric Acid, Hydroxypropyl Guar, Magnesium Chloride, Potassium Chloride, Purified Water, Sodium Chloride, Zinc Chloride

PACKAGE LABEL

Enter section text here